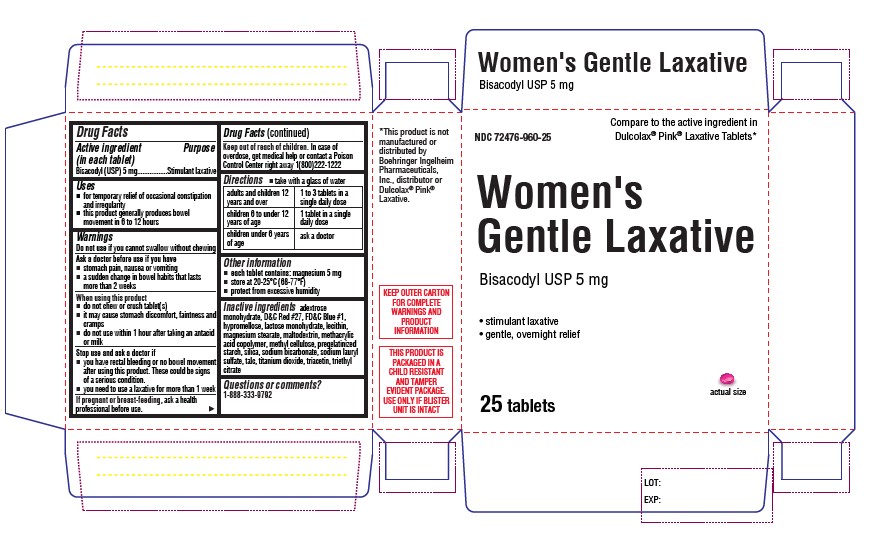 DRUG LABEL: Womens Gentle Laxative
NDC: 72476-960 | Form: TABLET, DELAYED RELEASE
Manufacturer: RETAIL BUSINESS SERVICES, LLC
Category: otc | Type: HUMAN OTC DRUG LABEL
Date: 20230502

ACTIVE INGREDIENTS: BISACODYL 5 mg/1 1
INACTIVE INGREDIENTS: HYPROMELLOSES; LACTOSE MONOHYDRATE; LECITHIN, SOYBEAN; MAGNESIUM STEARATE; MALTODEXTRIN; AMMONIUM ACRYLOYL DIMETHYLTAURATE/METHACRYLATE, DIMETHYLACRYLAMIDE AND METHACRYLIC ACID COPOLYMER, PPG-3 GLYCERYL TRIACRYLATE CROSSLINKED (100000 MW); HYDROXYMETHYL CELLULOSE; STARCH, POTATO; SILICA DIMETHYL SILYLATE; SODIUM BICARBONATE; SODIUM LAURYL SULFATE; TALC; TITANIUM DIOXIDE; TRIACETIN; TRIETHYL CITRATE; DEXTROSE MONOHYDRATE; D&C RED NO. 27; FD&C BLUE NO. 1

Women's Gentle Laxative

Active Ingredient (in each softgel)

Bisacodyl (USP) 5 mg

Purpose

Stimulant laxative

Uses

- for temporary relief of occasional constipation and irregularity
- this product generally produces bowel movement in 6 to 12 hours

Warnings

Do not use if you cannot swallow without chewing

Ask a doctor before use if you have

- stomach pain, nausea or vomiting
- a sudden change in bowel habits that lasts more than 2 weeks

When using this product

- do not chew or crush tablet(s)
- it may cause stomach discomfort, faintness and cramps
- do not use within 1 hour after taking an antacid or milk

Stop use and ask a doctor if

- you have rectal bleeding or no bowel movement after using this product. These could be signs of a serious condition.
- you need to use a laxative for more than 1 week

PREGNANCY OR BREAST FEEDING

If pregnant or breast-feeding, ask a health professional before use.

Keep out of reach of children. In case of overdose, get medical help or contact a Poison Control Center right away 1(800)222-1222

Directions

adults and children 12 years and over | 1 to 3 tablets in a single daily dose
children 6 to under 12 years of age | 1 tablet in a single daily dose
children under 6 years of age | ask a doctor

Other Information

- store at 20-25°C (68-77°F)
- protect from excessive humidity

Inactive ingredients

dextrose monohydrate, D&C Red #27, FD&C Blue #1, hypromellose, lactose monohydrate, lecithin, magnesium stearate, maltodextrin, methacrylic acid copolymer, methyl cellulose, pregelatinized starch, silica, sodium bicarbonate, sodium lauryl sulfate, talc, titanium dioxide, triacetin, triethyl citrate

Questions or comments?

1-888-333-9792

PACKAGE LABEL

Principal Display Panel

Carton